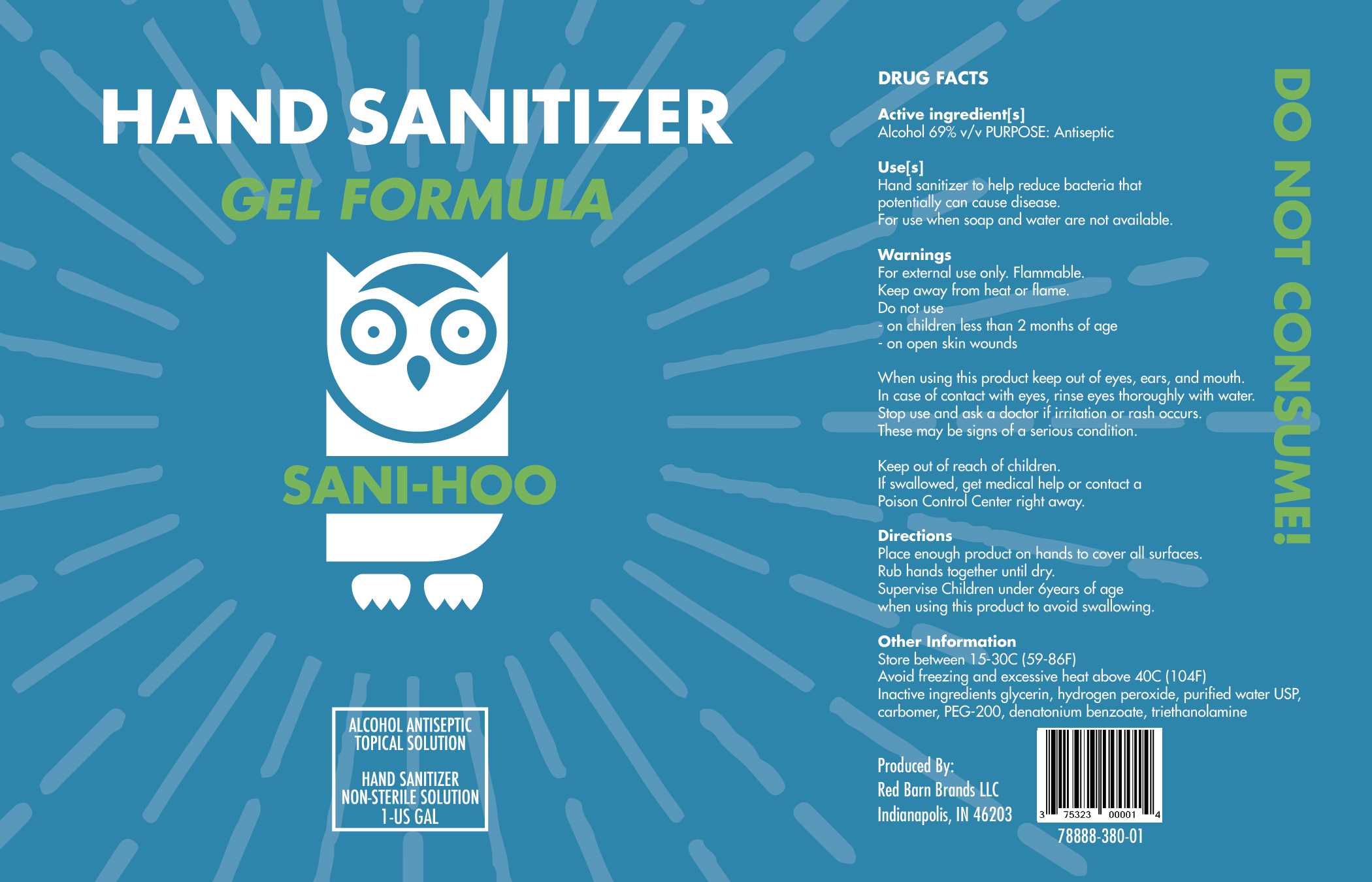 DRUG LABEL: SaniHoo Gel Hand Sanitizer
NDC: 78888-380 | Form: GEL
Manufacturer: Red Barn Brands, LLC
Category: otc | Type: HUMAN OTC DRUG LABEL
Date: 20200708

ACTIVE INGREDIENTS: ALCOHOL 69 mL/100 mL
INACTIVE INGREDIENTS: GLYCERIN 1.5 mL/100 mL; CARBOMER HOMOPOLYMER, UNSPECIFIED TYPE 0.5 g/100 mL; WATER 24.75 mL/100 mL; POLYETHYLENE GLYCOL, UNSPECIFIED 2 mL/100 mL; TROLAMINE 0.09 mL/100 mL; CYMBOPOGON CITRATUS LEAF 0.5 mL/100 mL; HYDROGEN PEROXIDE 0.125 mL/100 mL

Active Ingredient(s)

Alcohol 69% v/v. Purpose: Antiseptic

Purpose

Antiseptic, Hand Sanitizer

Use

Hand Sanitizer to held reduce bacteria that potentially can cause disease. For use when soap and water are not available.

Warnings

For external use only. Flammable. Keep away from heat or flame.

Do not use

on children less than 2 months of age

on open skin wounds

When using this product keep out of eyes, ears, and mouth. In case of contact with eyes, rinse eyes thoroughly with water.

Stop use and ask a doctor if irritation or rash occurs. These may be signs of a serious condition.

Keep out of reach of children. If swallowed, get medical help or contact a Poison Control Center right away.

Stop use and ask a doctor if irritation or rash occurs. These may be signs of a serious condition.

Keep out of reach of children. If swallowed, get medical help or contact a Poison Control Center right away.

Directions

Place enough product on hands to cover all surfaces. Rub hands together to dry.

Supervise children under 6 years of age when using this product to avoid swallowing.

Other information

Store between 15-30C (59-86F)

Avoid freezing and excessive heat above 40C (104F)

Inactive ingredients

glycerin, hydrogen peroxide, purified water USP, carbomer, PEG-200, denatonium benzoate, triethanolamine

Package Label - Principal Display Panel

3785.41 mL NDC: 78888-380-01